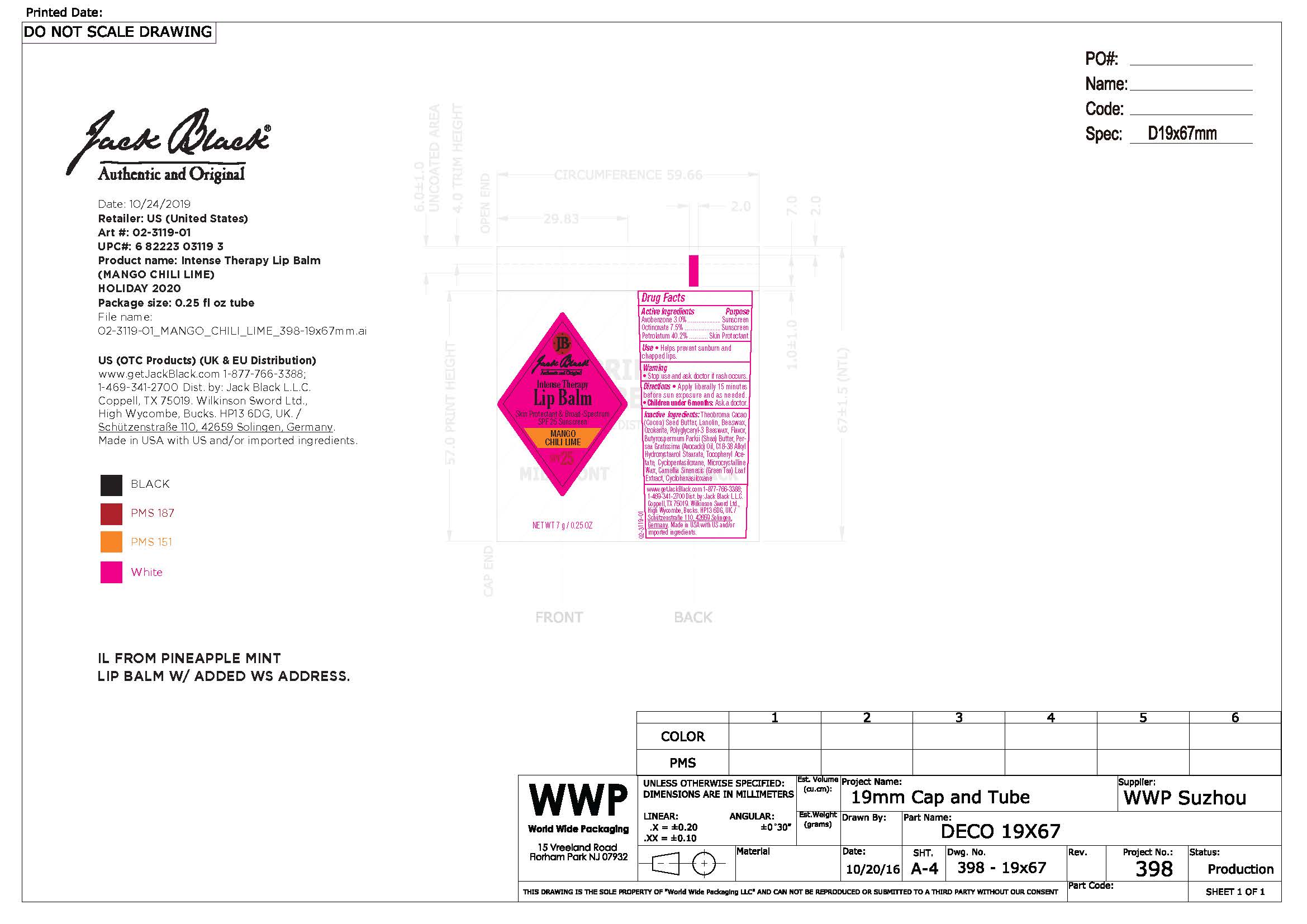 DRUG LABEL: Jack Black Intensive Therapy Lip Balm Mango Chili Lime
NDC: 66738-063 | Form: OINTMENT
Manufacturer: Jack Black, LLC
Category: otc | Type: HUMAN OTC DRUG LABEL
Date: 20231108

ACTIVE INGREDIENTS: AVOBENZONE 30 g/1000 g; octinoxate 75 g/1000 g; PETROLATUM 402 g/1000 g
INACTIVE INGREDIENTS: COCOA BUTTER; LANOLIN; YELLOW WAX; CERESIN; SHEA BUTTER; AVOCADO OIL; .ALPHA.-TOCOPHEROL ACETATE; CYCLOMETHICONE 5; MICROCRYSTALLINE WAX; CAMELLIA SINENSIS WHOLE; CYCLOMETHICONE 6

Jack Black Intensive Therapy Lip Balm Mango Chili Lime

Warnings

Stop use and ask a doctor if rash occurs.

Keep out of Reach of Children

Active Ingredients

Avobenzone 3.0% sunscreen

Octinoxate 7.5% sunscreen

Petrolatum 40.2% skin protectant

Uses

Helps prevent sunburn and chapped lips

Uses

Helps prevent sunburn and chapped lips.

Directions

Apply liberally 15 minutes before sun exposure and as needed. Children under 6 months: ask a doctor.

Inactive Ingredients

theobroma cacao (coca) seed butter, lanolin, beeswax, ozokerite, polyglyceryl-3 beeswax, flavor, butyrospermum parkii (shea) butter, persea gratissima (avocado) oil, C18-38 alkyl hydroxystearol stearate, tocopheryl acetate, cyclopentasiloxane, microcrystalline wax, camellia sinenesis (green tea) leaf extract, cyclohexasiloxane

Questions

www.getjackblack.com

1-877-766-3388